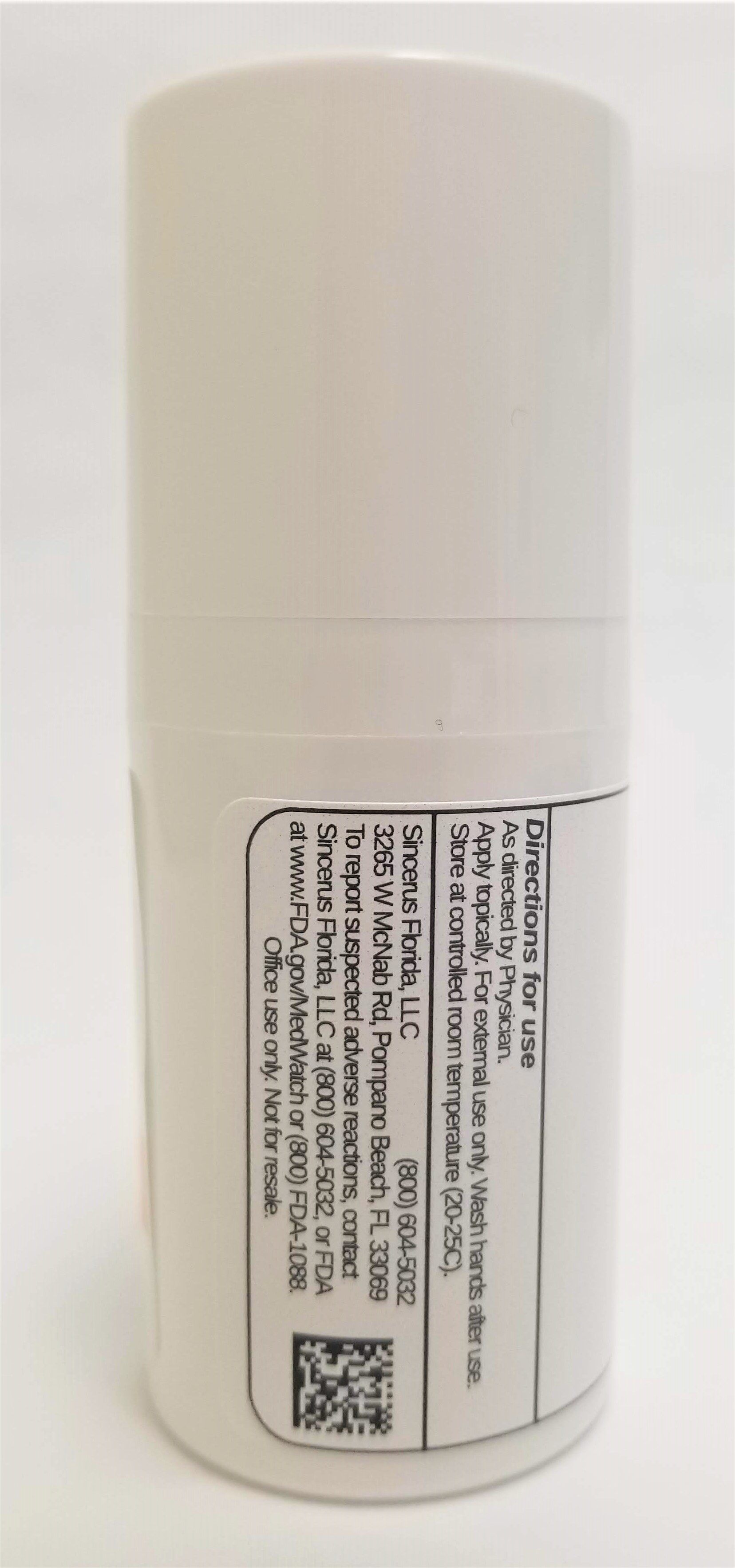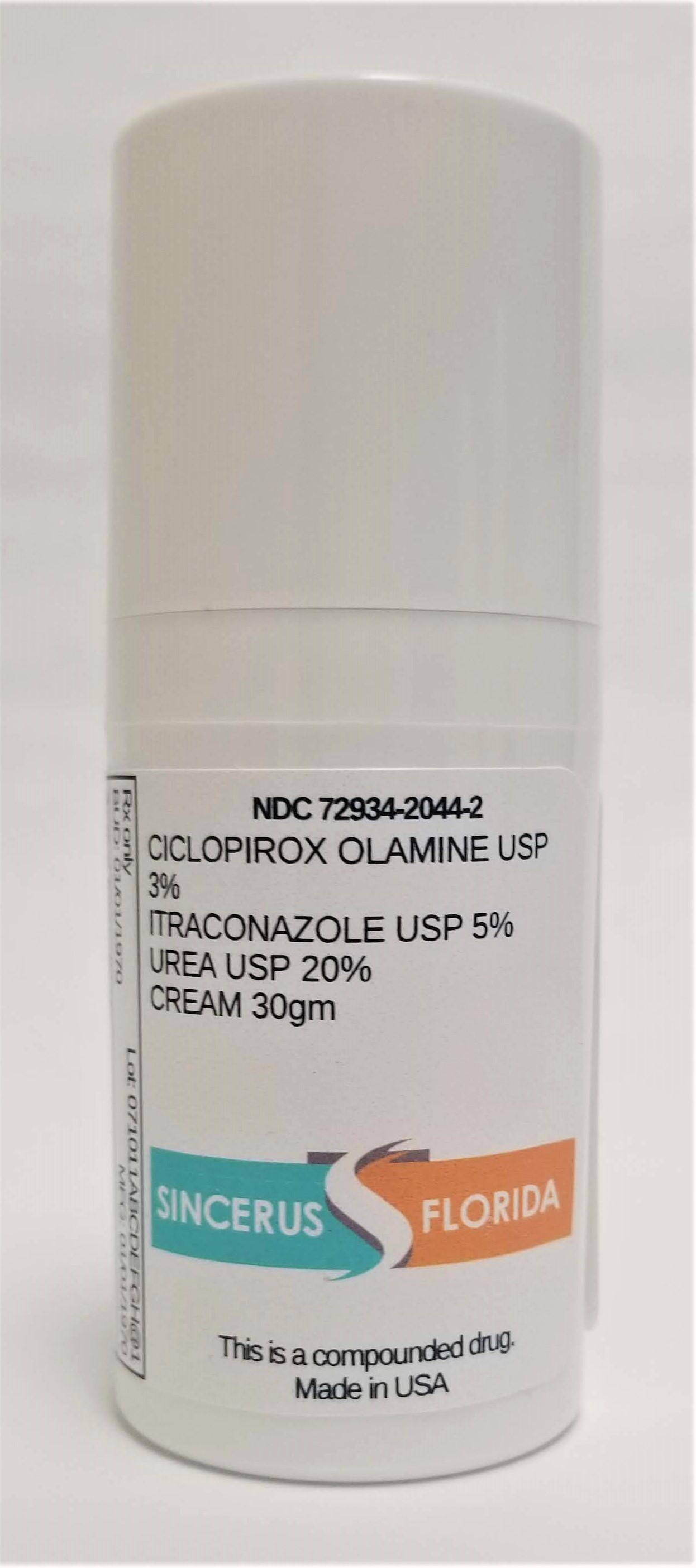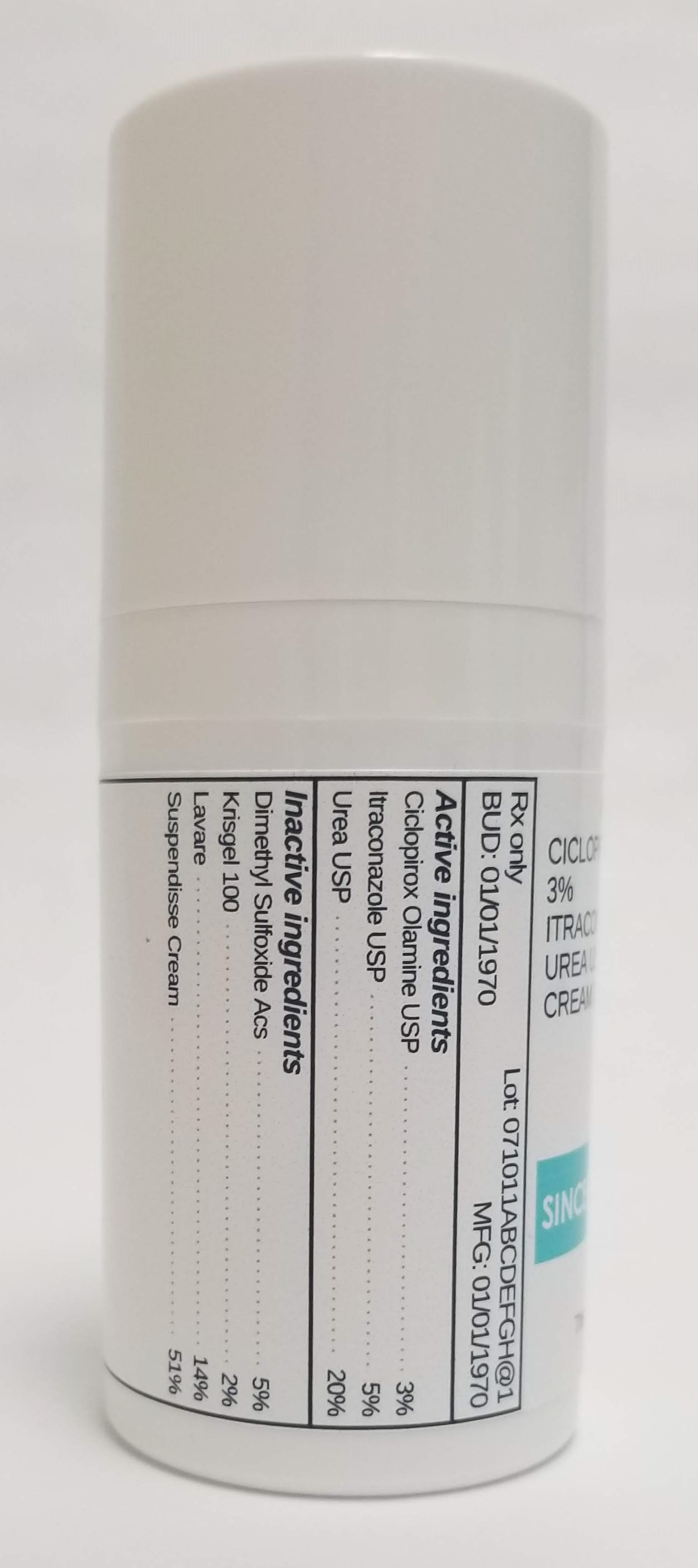 DRUG LABEL: CICLOPIROX 3% / ITRACONAZOLE 5% / UREA 20%
NDC: 72934-2044 | Form: CREAM
Manufacturer: Sincerus Florida, LLC
Category: prescription | Type: HUMAN PRESCRIPTION DRUG LABEL
Date: 20190520

ACTIVE INGREDIENTS: CICLOPIROX OLAMINE 3 g/100 g; ITRACONAZOLE 5 g/100 g; UREA 20 g/100 g

CICLOPIROX 3% / ITRACONAZOLE 5% / UREA 20%